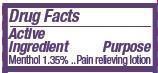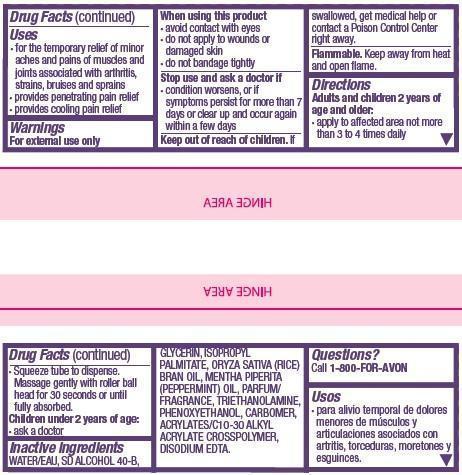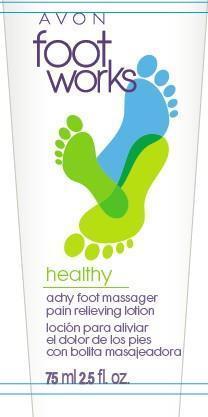 DRUG LABEL: Foot Works
NDC: 10096-0288 | Form: LOTION
Manufacturer: New Avon LLC
Category: otc | Type: HUMAN OTC DRUG LABEL
Date: 20160217

ACTIVE INGREDIENTS: MENTHOL 13.5 mg/1 mL

Active ingredient
Menthol 1.35%................

Purpose

.........Pain relieving lotion

Uses
• for the temporary relief of minor aches and pains of muscles and joints associated with arthritis, strains, bruises and sprains
• provides penetrating pain relief
• provides cooling pain relief

Warnings
For external use only

When using this product
• avoid contact with the eyes
• do not apply to wounds or damaged skin
• do not bandage tightly

Stop use and ask a doctor if
• condition worsens, or if symptoms persist for more than 7 days or clear up and occur again within a few days

Keep out of reach of children. If swallowed, get medical help or contact a Poison Control Center right away.

Directions
Adults and children 2 years of age and older:
• apply to affected area not more than 3 to 4 times daily

•Squeeze tube to dispense. Massage gently with roller ball head for 30 seconds or until fully absorbed.
Children under 2 years of age:
• consult a doctor

Inactive ingredients

WATER/EAU, SD ALCOHOL 40-B, GLYCERIN, ISOPROPYL PALMITATE, ORYZA SATIVA (RICE) BRAN OIL, MENTHA PIPERITA (PEPPERMINT) OIL, PARFUM/FRAGRANCE, TRIETHANOLAMINE, PHENOXYETHANOL, CARBOMER, ACRYLATES/C10-30 ALKYL ACRYLATE CROSSPOLYMER, DISODIUM EDTA.

Questions?

Call 1-800-FOR AVON